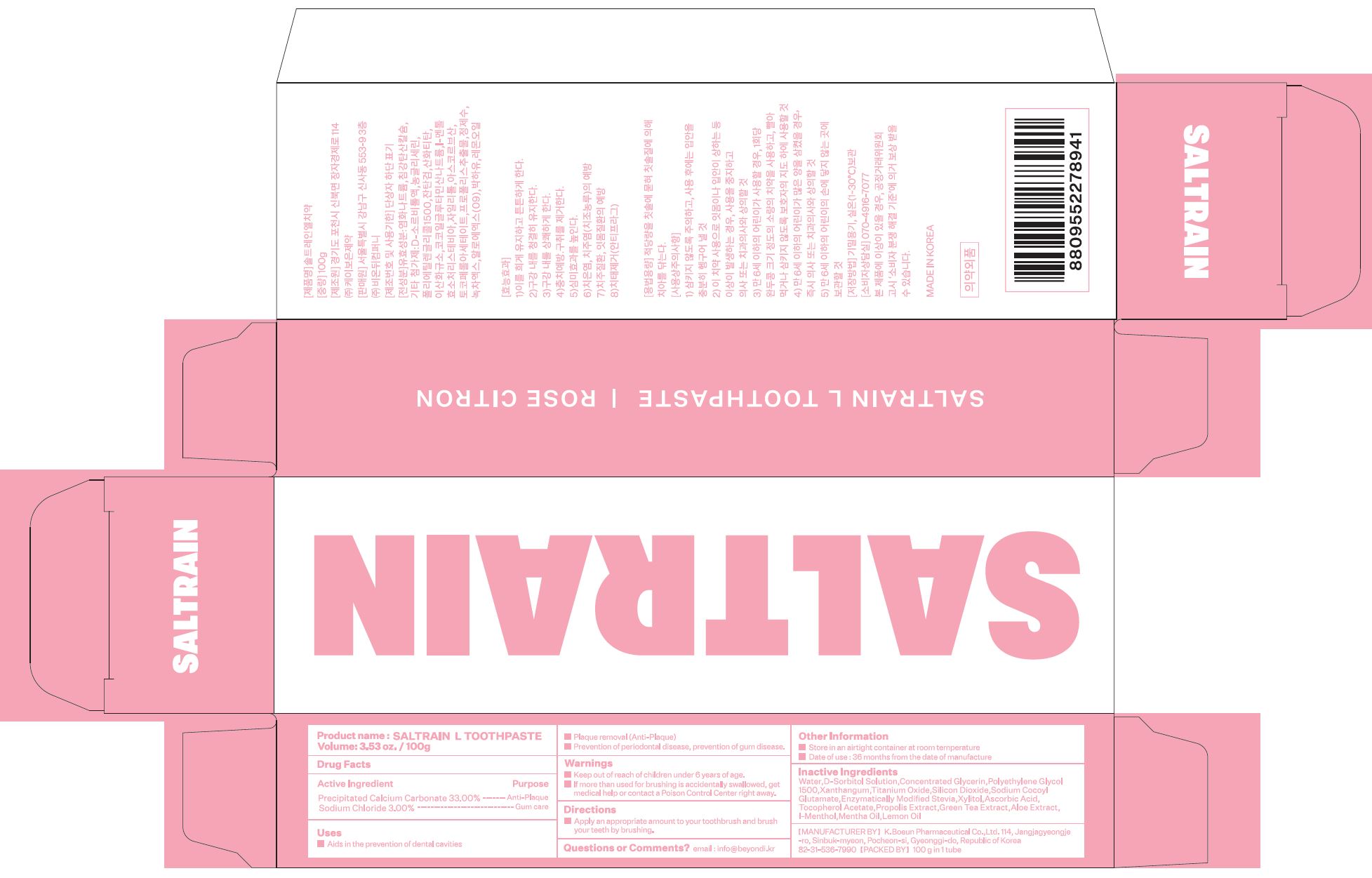 DRUG LABEL: SALTRAIN LTOOTHPASTE
NDC: 74724-0031 | Form: PASTE, DENTIFRICE
Manufacturer: K.Boeun Pharmaceutical Co.,Ltd.
Category: otc | Type: HUMAN OTC DRUG LABEL
Date: 20221231

ACTIVE INGREDIENTS: SODIUM CHLORIDE 3 g/100 g; CALCIUM CARBONATE 33 g/100 g
INACTIVE INGREDIENTS: XYLITOL; WATER

ACTIVE INGREDIENT

Sodium Chloride, Precipitated Calcium Carbonate

INACTIVE INGREDIENT

D-Sorbitol Solution
Concentrated Glycerin
Polyethylene Glycol 1500
Xanthan gum
Titanium Oxide
Silicon Dioxide
Sodium Cocoyl Glutamate
Enzymatically Modified Stevia
Xylitol
Ascorbic Acid
Tocopherol Acetate
Propolis Extract
Green Tea Extract

Aloe Extract
l-Menthol
Mentha Oil
Lemon Oil
Water

PURPOSE

aids in the prevention of dental cavities

plaque removal (anti-plaque)

prevention of periodontal disease, prevention of gum disease

Keep out of reach of children

INDICATIONS AND USAGE

Apply an appropriate amount to your toothbrush and brush your teeth by brushing.

Warnings

Keep out of reach of children

■ If more than used for rinsing is accidentally swallowed, get medical help or contact a Poison Control Center right away.

Other Information

■ Store in an airtight container at room temperature

■ Date of use : 36 months from the date of manufacture

DOSAGE AND ADMINISTRATION

For dental use only